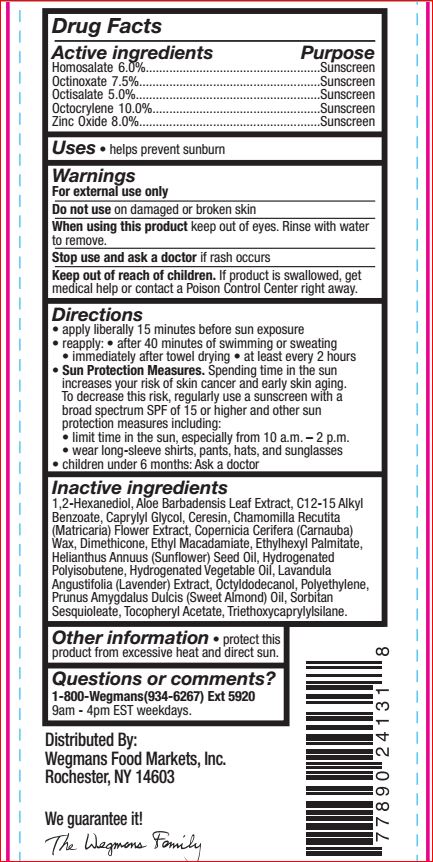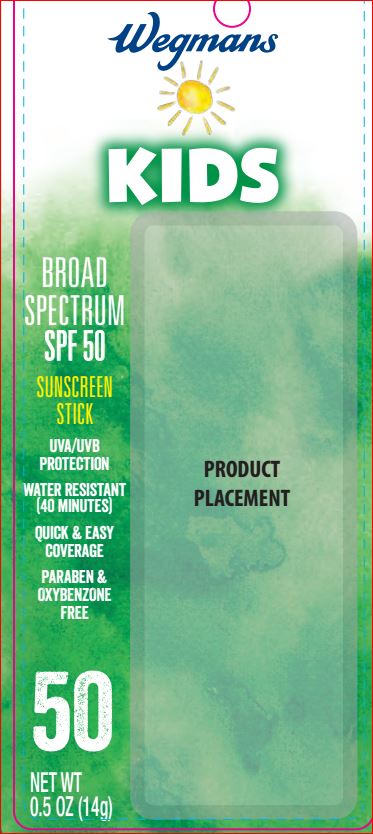 DRUG LABEL: Kids Sunscreen SPF 50
NDC: 47124-338 | Form: STICK
Manufacturer: Wegman
Category: otc | Type: HUMAN OTC DRUG LABEL
Date: 20180122

ACTIVE INGREDIENTS: Homosalate 6 g/100 g; Octinoxate 7.5 g/100 g; Octisalate 5 g/100 g; Octocrylene 10 g/100 g; Zinc Oxide 8 g/100 g
INACTIVE INGREDIENTS: 1,2-Hexanediol; Aloe; ALKYL (C12-15) BENZOATE; Caprylyl Glycol; Ceresin; CARNAUBA WAX; Dimethicone; Ethyl Macadamiate; Ethylhexyl Palmitate; HELIANTHUS ANNUUS SEED WAX; HYDROGENATED POLYBUTENE (1300 MW); LAVANDULA ANGUSTIFOLIA SUBSP. ANGUSTIFOLIA FLOWERING TOP; CHAMOMILE FLOWER OIL; Mineral Oil; Octyldodecanol; ALMOND OIL; Sorbitan Sesquioleate; .ALPHA.-TOCOPHEROL ACETATE; Triethoxycaprylylsilane

Drug Facts

Active ingredients Purpose

Homosalate 6.0%....................................................Sunscreen
Octinoxate 7.5%......................................................Sunscreen
Octisalate 5.0%.......................................................Sunscreen
Octocrylene 10.0%..................................................Sunscreen
Zinc Oxide 8.0%......................................................Sunscreen

INDICATIONS AND USAGE

Uses • helps prevent sunburn

INDICATIONS AND USAGE

Uses • helps prevent sunburn

Warnings

For external use only
Do not use on damaged or broken skin
When using this product keep out of eyes. Rinse with water to remove.
Stop use and ask a doctor if rash occurs
Keep out of reach of children. If product is swallowed, get medical help or contact a Poison Control Center right away.

Directions

• apply liberally 15 minutes before sun exposure
• reapply: • after 80 minutes of swimming or sweating
• immediately after towel drying • at least every 2 hours
• Sun Protection Measures. Spending time in the sun
increases your risk of skin cancer and early skin aging.
To decrease this risk, regularly use a sunscreen with a
broad spectrum SPF of 15 or higher and other sun
protection measures including:
• limit time in the sun, especially from 10 a.m. – 2 p.m.
• wear long-sleeve shirts, pants, hats, and sunglasses
• children under 6 months: Ask a doctor

Inactive ingredients

1,2-Hexanediol, Aloe Barbadensis Leaf Extract, C12-15 Alkyl
Benzoate, Caprylyl Glycol, Ceresin, Chamomilla Recutita
(Matricaria) Flower Extract, Copernicia Cerifera (Carnauba)
Wax, Dimethicone, Ethyl Macadamiate, Ethylhexyl Palmitate,
Helianthus Annuus (Sunflower) Seed Oil, Hydrogenated
Polyisobutene, Hydrogenated Vegetable Oil, Lavandula
Angustifolia (Lavender) Extract, Octyldodecanol, Polyethylene,
Prunus Amygdalus Dulcis (Sweet Almond) Oil, Sorbitan
Sesquioleate, Tocopheryl Acetate, Triethoxycaprylylsilane